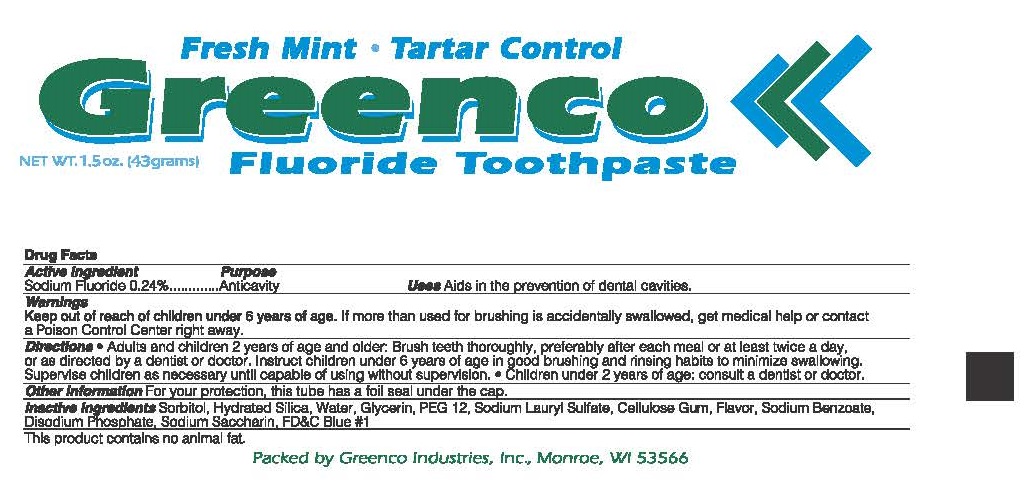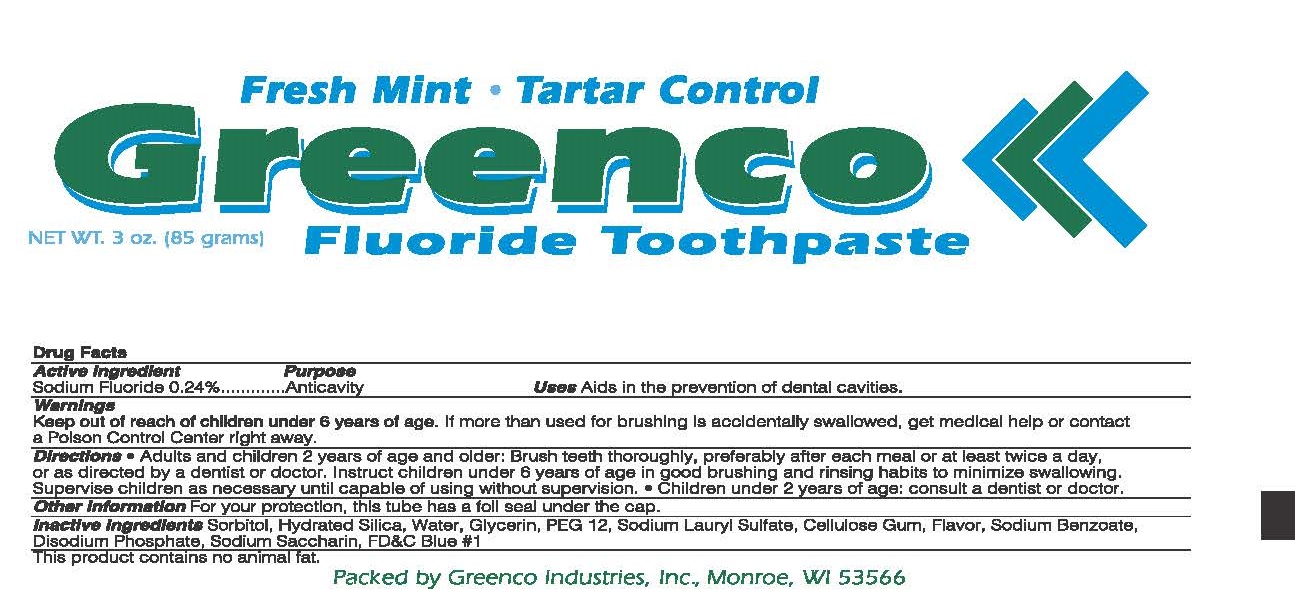 DRUG LABEL: Greenco
NDC: 63372-0596 | Form: PASTE, DENTIFRICE
Manufacturer: Greenco Industries, Inc.
Category: otc | Type: HUMAN OTC DRUG LABEL
Date: 20171206

ACTIVE INGREDIENTS: SODIUM FLUORIDE 2.4 mg/1 g
INACTIVE INGREDIENTS: SACCHARIN SODIUM; SODIUM BENTONITE; GLYCERIN; POLYETHYLENE GLYCOL 600; CARBOXYMETHYLCELLULOSE; SODIUM LAURYL SULFATE; SILICON DIOXIDE; WATER; SODIUM PHOSPHATE, DIBASIC, ANHYDROUS; SORBITOL; FD&C BLUE NO. 1

Greenco - Toothpaste

Active ingredient

Sodium Fluoride 0.24%

Purpose

Anticavity

Uses

Aids in the prevention of dental cavities.

Keep out of reach of children under 6 years of age. If more than used for brushing is accidentally swallowed, get medical help or contact a Poison Control Center right away.

Directions

- Adults and children 2 years of age and older: Brush teeth thoroughly, preferably after each meal or at least twice a day, or as directed by a dentist or doctor. Instruct children under 6 years of age in good brushing and rinsing habits to minimize swallowing. Supervise children as necessary until capable of using without supervision.
- Children under 2 years of age: consult a dentist or doctor.

Other informaiton

For your protection, this tube has a foil seal under the cap.

Inactive ingredients

Sorbitol, Hydrated Silica, Water, Glycerin, PEG 12, Sodium Lauryl Sulfate, Cellulose Gum, Flavor, Sodium Benzoate, Disodium Phosphate, Sodium Saccharin, FD&C Blue #1

Principal Display Panel

Fresh Mint Tartar Control

Greenco

NET WT. 1.5oz. (43grams) Fluoride Toothpaste